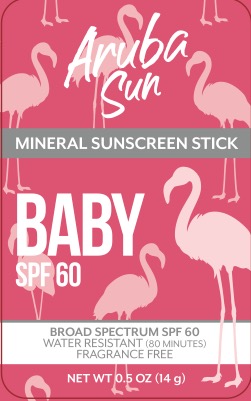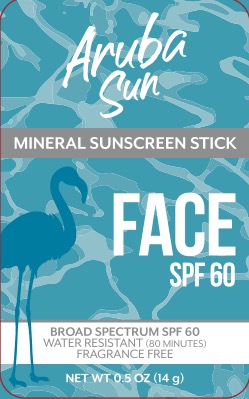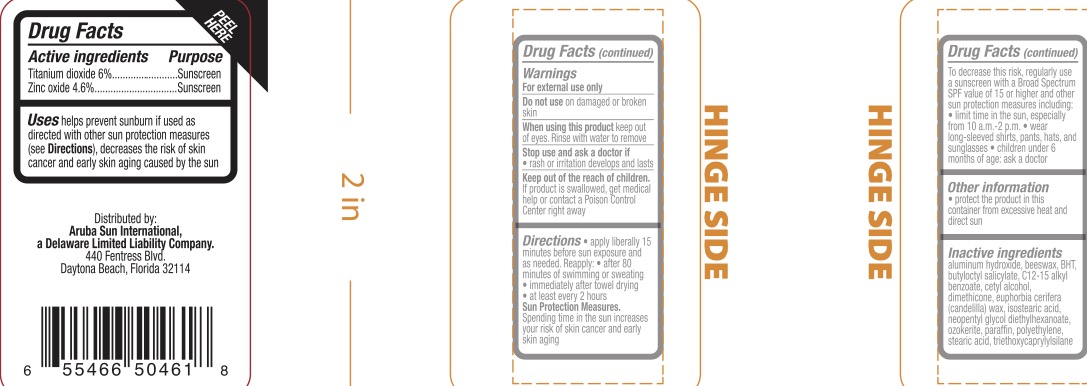 DRUG LABEL: SPF 60 Mineral Sunscreen
NDC: 72839-547 | Form: STICK
Manufacturer: Derma Care Research Labs, LLC
Category: otc | Type: HUMAN OTC DRUG LABEL
Date: 20231121

ACTIVE INGREDIENTS: TITANIUM DIOXIDE 6 g/100 g; ZINC OXIDE 4.6 g/100 g
INACTIVE INGREDIENTS: CANDELILLA WAX; NEOPENTYL GLYCOL DIETHYLHEXANOATE; CERESIN; HIGH DENSITY POLYETHYLENE; STEARIC ACID; ALUMINUM HYDROXIDE; SYNTHETIC BEESWAX; BUTYLATED HYDROXYTOLUENE; BUTYLOCTYL SALICYLATE; ALKYL (C12-15) BENZOATE; CETYL ALCOHOL; DIMETHICONE 200; ISOSTEARIC ACID; PARAFFIN; TRIETHOXYCAPRYLYLSILANE

Aruba SPF 60 Sunscreen Stick

ACTIVE INGREDIENT

Titanium Dioxide 6%, Zinc Oxide 4.6%

PURPOSE

Sunscreen

INDICATIONS AND USAGE

Helps prevent sunburn if used as directed with other sun protection measures (see Directions), decreases the risk of skin cancer and early skin aging caused by the sun.

WARNINGS

For external use only.

Do not use on damaged or broken skin.

When using this product keep out of eyes. Rinse with water to remove.

Stop use and ask a doctor if rash or irritation develops and lasts.

KEEP OUT OF REACH OF CHILDREN

If product is swallowed, get medical help or contact a Poison Control Center right away.

DOSAGE AND ADMINISTRATION

Apply liberally 15 minutes before sun exposure and as needed. Reapply

- after 80 minutes of swimming or sweating
- immediately after towel drying
- at least every 2 hours

Sun Protection Measures. Spending time in the sun increases your risk of skin cancer and early skin aging. To decrease this risk, regularly use a sunscreen with a Broad Spectrum value of 15 or higher and other sun protection measures including:

- limit time in the sun, especially from 10:00 a.m. - 2:00 p.m.
- wear long-sleeved shirts, pants, hats, and sunglasses
- Children under 6 months of age: ask a doctor.

INACTIVE INGREDIENT

Aluminum hydroxide, beeswax, BHT, butyloctyl salicylate, C12-15 alkyl benzoate, cetyl alcohol, dimethicone, euphoria cerifera (candelilla) wax, isostearic acid, neopentyl glycol diethylhexanoate, ozokerite, paraffin, polyethylene, stearic acid, triethoxycaprylysilane